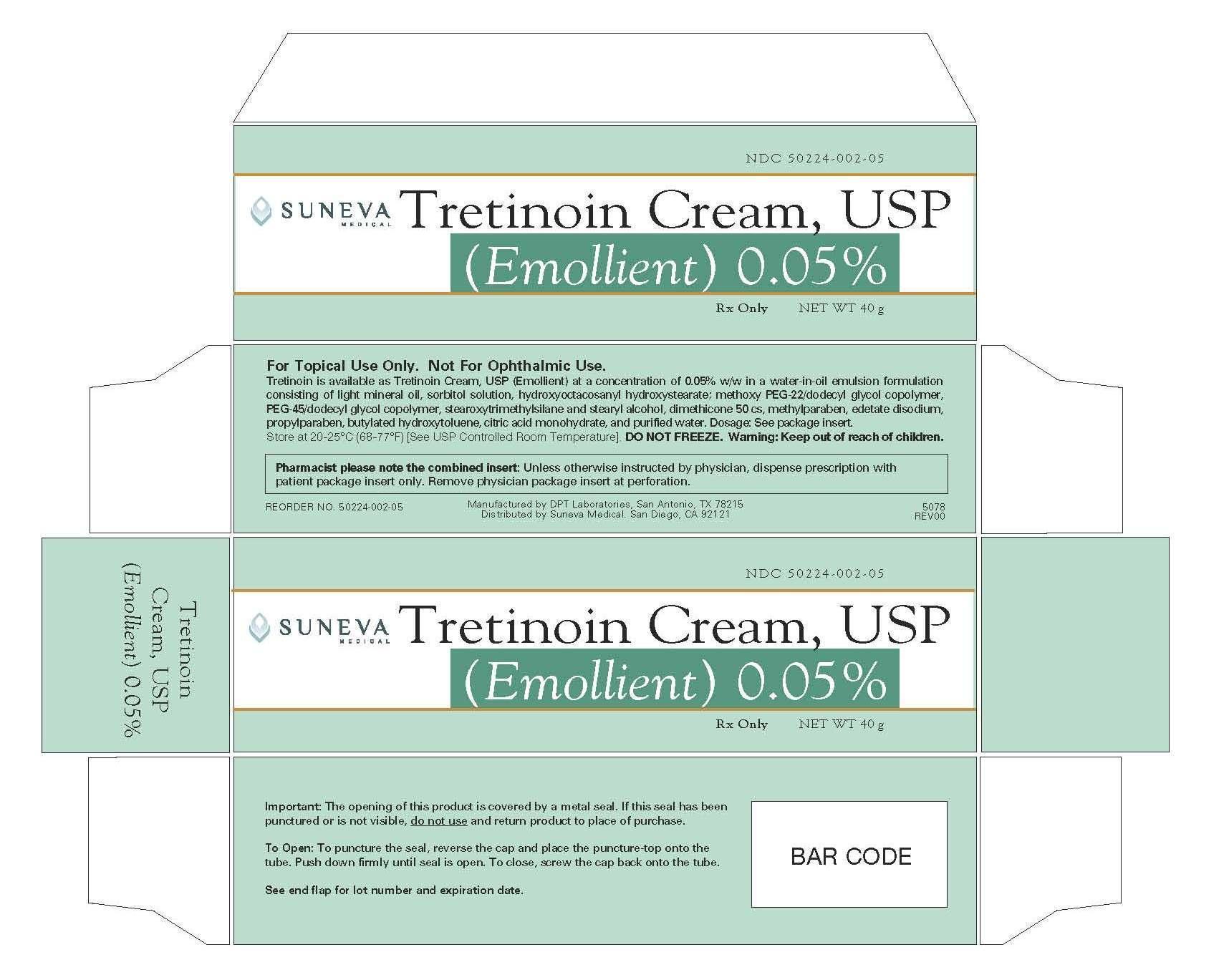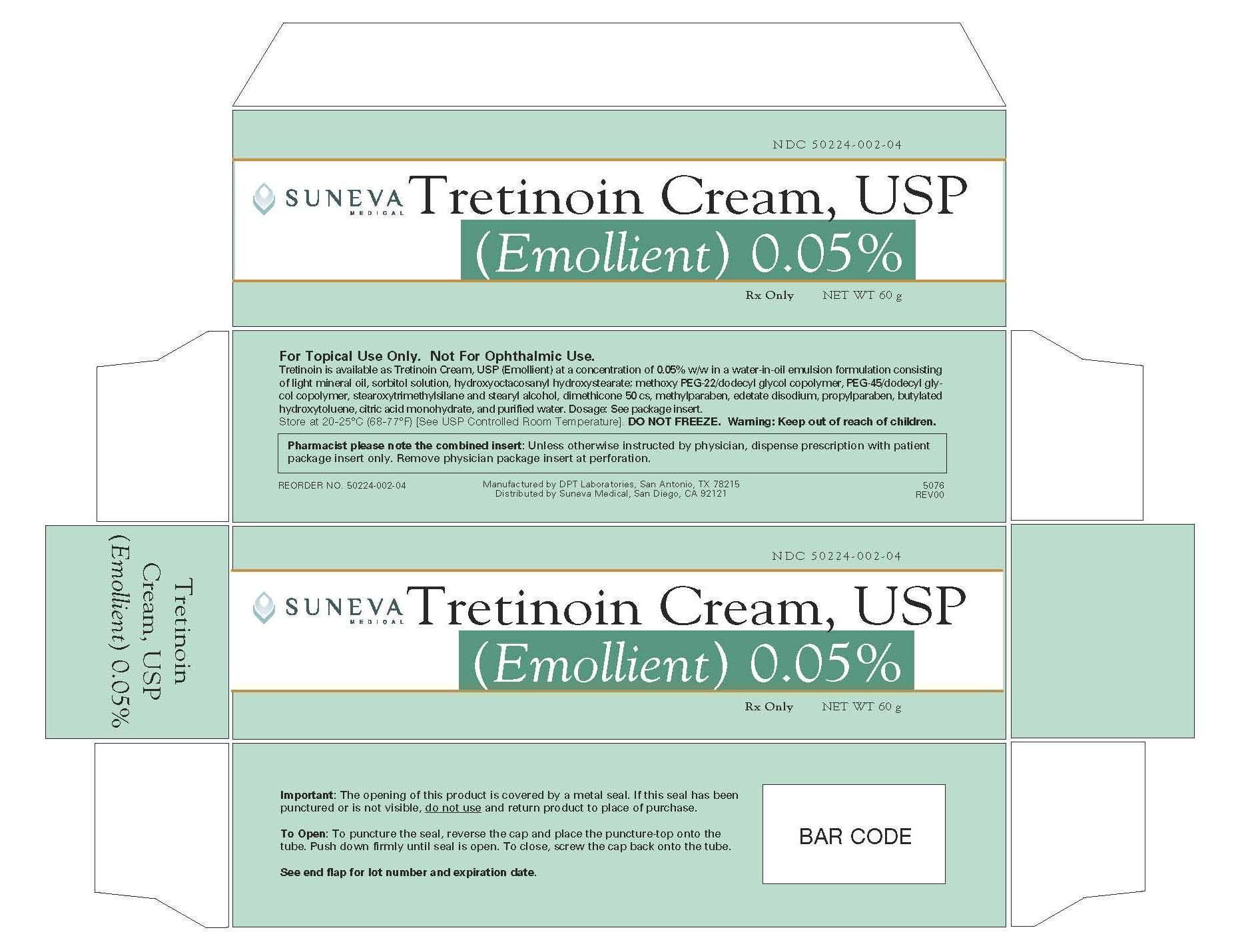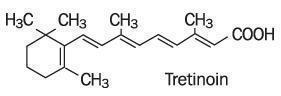 DRUG LABEL: Refissa
NDC: 50224-002 | Form: CREAM
Manufacturer: Suneva Medical, Inc.
Category: prescription | Type: HUMAN PRESCRIPTION DRUG LABEL
Date: 20120828

ACTIVE INGREDIENTS: TRETINOIN 0.5 mg/1 g
INACTIVE INGREDIENTS: BUTYLATED HYDROXYTOLUENE; CITRIC ACID MONOHYDRATE; EDETATE DISODIUM; LIGHT MINERAL OIL; DIMETHICONE; METHYLPARABEN; PROPYLPARABEN; WATER; SORBITOL

Tretinoin Cream, USP (Emollient) 0.05%

DESCRIPTION

Tretinoin Cream, USP (Emollient) 0.05% contains the active ingredient tretinoin in a cream base. Tretinoin is a yellow-to-light-orange crystalline powder having a characteristic floral odor. Tretinoin is soluble in dimethylsulfoxide, slightly soluble in polyethylene glycol 400, octanol, and 100% ethanol. It is practically insoluble in water and mineral oil, and it is insoluble in glycerin. The chemical name for tretinoin is (all-E)-3,7-dimethyl-9-(2,6,6-trimethyl-1-cyclonexen-1-yl)-2,4,6,8-nonatetraenoic acid. Tretinoin is also referred to as all-trans-retinoic acid and has a molecular weight of 300.44. The structural formula is represented below.

Tretinoin is available as Tretinoin Cream, USP (Emollient) at a concentration of 0.05% w/w in a water-in-oil emulsion formulation consisting of butylated hydroxytoluene, citric acid monohydrate, dimethicone 50 cs, edetate disodium, fragrance, hydroxyoctacosanyl hydroxystearate, light mineral oil, methoxy PEG-22/dodecyl glycol copolymer, methylparaben, PEG-45/dodecyl glycol copolymer, purified water, quaternium-15, stearoxytrimethylsilane and stearyl alcohol, and sorbitol solution.

CLINICAL PHARMACOLOGY

Tretinoin is an endogenous retinoid metabolite of Vitamin A that binds to intracellular receptors in the cytosol and nucleus, but cutaneous levels of tretinoin in excess of physiologic concentrations occur following application of a tretinoin-containing topical drug product. Although tretinoin activates three members of the retinoic acid (RAR) nuclear receptors (RARa, RARb, and RARg) which may act to modify gene expression, subsequent protein synthesis, and epithelial cell growth and differentiation, it has not been established whether the clinical effects of tretinoin are mediated through activation of retinoic acid receptors, other mechanisms such as irritation, or both.

The effect of tretinoin on skin with chronic photodamage has not been evaluated in animal studies. When hairless albino mice were treated topically with tretinoin shortly after a period of UVB irradiation, new collagen formation was demonstrated only in photodamaged skin. However, in human skin treated topically, adequate data have not been provided to demonstrate any increase in desmosine, hydroxyproline, or elastin mRNA. Application of 0.1% tretinoin cream to photodamaged human forearm skin was associated with an increase in antibody staining for procollagen I propeptide. No correlation was made between procollagen I propeptide staining with collagen I levels or with observed clinical effects. Thus, the relationships between the increased collagen in rodents, increased procollagen I propeptide in humans, and the clinical effects of tretinoin have not yet been clearly defined.

Tretinoin was shown to enhance UV-stimulated melanogenesis in pigmented mice. Generalized amyloid deposition in the basal layer of tretinoin-treated skin was noted in a two-year mouse study. In a different study, hyalinization at tretinoin-treated skin sites was noted at doses beginning at 0.25 mg/kg in CD-1 mice.

The transdermal absorption of tretinoin from various topical formulations ranged from 1% to 31% of applied dose, depending on whether it was applied to healthy skin or dermatitic skin. When percutaneous absorption of Tretinoin Cream, USP (Emollient) 0.05% was assessed in healthy male subjects (n=14), as well as after repeated daily applications for 28 days, the absorption of tretinoin was less than 2% and endogenous concentrations of tretinoin and its major metabolites were unaltered.

INDICATIONS AND USAGE

(To understand fully the indication for this product, please read the entire INDICATIONS AND USAGE section of the labeling.)

Tretinoin Cream, USP (Emollient) 0.05% is indicated as an adjunctive agent (see second bullet point below) for use in the mitigation (palliation) of fine wrinkles, mottled hyperpigmentation, and tactile roughness of facial skin in patients who use comprehensive skin care and sunlight avoidance programs (see bullet 3 for populations in which effectiveness has not been established). TRETINOIN CREAM, USP (EMOLLIENT) DOES NOT ELIMINATE WRINKLES, REPAIR SUN-DAMAGED SKIN, REVERSE PHOTOAGING, or RESTORE MORE YOUTHFUL or YOUNGER SKIN. In double-blinded, vehicle-controlled clinical studies, many patients in the vehicle group achieved desired palliative effects on fine wrinkling, mottled hyperpigmentation, and tactile roughness of facial skin with the use of comprehensive skin care and sunlight avoidance programs including sunscreens, protective clothing, and non-prescription emollient creams.

- Tretinoin Cream, USP (Emollient) 0.05% has NOT DEMONSTRATED A MITIGATING EFFECT on significant signs of chronic sun exposure such as coarse or deep wrinkling, skin yellowing, lentigines, telangiectasia, skin laxity, keratinocytic atypia, melanocytic atypia, or dermal elastosis.
- Tretinoin Cream, USP (Emollient) 0.05% should be used under medical supervision as an adjunct to a comprehensive skin care and sunlight avoidance program that includes the use of effective sunscreens (minimum SPF of 15) and protective clothing when desired results on fine wrinkles, mottled hyperpigmentation, and roughness of facial skin have not been achieved with a comprehensive skin care and sunlight avoidance program alone.
- The effectiveness of Tretinoin Cream, USP (Emollient) 0.05% in the mitigation of fine wrinkles, mottled hyperpigmentation, and tactile roughness of facial skin has not been established in people greater than 50 years of age OR in people with moderately to heavily pigmented skin. In addition, patients with visible actinic keratoses and patients with a history of skin cancer were excluded from clinical trials of Tretinoin Cream, USP (Emollient) 0.05%. Thus the effectiveness and safety of Tretinoin Cream, USP (Emollient) 0.05% in these populations are not known at this time.
- Neither the safety nor the effectiveness of Tretinoin Cream, USP (Emollient) for the prevention or treatment of actinic keratoses or skin neoplasms has been established.
- Neither the safety nor the efficacy of using Tretinoin Cream, USP (Emollient) 0.05% daily for greater than 48 weeks has been established, and daily use beyond 48 weeks has not been systematically and histologically investigated in adequate and well-controlled trials. (see WARNINGS section.)

CLINICAL TRIALS

Two adequate and well-controlled trials were conducted involving a total of 161 evaluable patients (under 50 years of age) treated with Tretinoin Cream, USP (Emollient) 0.05% and 154 evaluable patients treated with the vehicle cream on the face for 24 weeks as an adjunct to a comprehensive skin care and sun-avoidance program, to assess the effects on fine wrinkling, mottled hyperpigmentation, and tactile skin roughness. Patients were evaluated at baseline on a 10-point scale, and changes from that baseline rating were categorized as follows:

No Improvement: No change or an increase of 1 unit or more
Minimal Improvement: Reduction of 1 unit
Moderate Improvement: Reduction of 2 units or more

In these trials, the fine wrinkles, mottled hyperpigmentation, and tactile roughness of the facial skin were thought to be caused by multiple factors which included intrinsic aging or environmental factors, such as chronic sunlight exposure.

The results of these assessments are as follows:

FINE WRINKLING
 | NO IMPROVEMENT | MINIMAL IMPROVEMENT | MODERATE IMPROVEMENT
Tretinoin Cream, USP (Emollient) 0.05% + CSP* | 36% | 40% | 24%
Vehicle + CSP | 62% | 30% | 8%
MOTTLED HYPERPIGMENTATION
 | NO IMPROVEMENT | MINIMAL IMPROVEMENT | MODERATE IMPROVEMENT
Tretinoin Cream, USP (Emollient) 0.05% + CSP* | 35% | 27% | 38%
Vehicle + CSP | 53% | 21% | 27%
TACTILE SKIN ROUGHNESS
 | NO IMPROVEMENT | MINIMAL IMPROVEMENT | MODERATE IMPROVEMENT
Tretinoin Cream, USP (Emollient) 0.05% + CSP* | 49% | 35% | 16%
Vehicle + CSP | 67% | 23% | 10%
*CSP= Comprehensive skin protection and sun-avoidance programs included use of sunscreens, protective clothing, and non-prescription emollient creams.

Most of the improvement in these signs was noted during the first 24 weeks of therapy. Thereafter, therapy primarily maintained the improvement realized during the first 24 weeks.

A majority of patients will lose most mitigating effects of Tretinoin Cream, USP (Emollient) 0.05% on fine wrinkles, mottled hyperpigmentation, and tactile roughness of facial skin with discontinuation of a comprehensive skin care and sunlight avoidance program including Tretinoin Cream, USP (Emollient) 0.05%; however, the safety and effectiveness of using Tretinoin Cream, USP (Emollient) 0.05% daily for greater than 48 weeks have not been established.

CONTRAINDICATIONS

This drug is contraindicated in individuals with a history of sensitivity reactions to any of its components. It should be discontinued if hypersensitivity to any of its ingredients is noted.

WARNINGS

- Tretinoin Cream, USP (Emollient) is a dermal irritant, and the results of continued irritation of the skin for greater than 48 weeks in chronic use with Tretinoin Cream, USP (Emollient) are not known. There is evidence of atypical changes in melanocytes and keratinocytes, and of increased dermal elastosis in some patients treated with Tretinoin Cream, USP (Emollient) for longer than 48 weeks. The significance of these findings is unknown.
- Safety and effectiveness of Tretinoin Cream, USP (Emollient) 0.05% in individuals with moderately or heavily pigmented skin have not been established.
- Tretinoin Cream, USP (Emollient) should not be administered if the patient is also taking drugs known to be photosensitizers (e.g., thiazides, tetracyclines, fluoroquinolones, phenothiazines, sulfonamides) because of the possibility of augmented phototoxicity.

Exposure to sunlight (including sunlamps) should be avoided or minimized during use of Tretinoin Cream, USP (Emollient), because of heightened sunburn susceptibility. Patients should be warned to use sunscreens (minimum SPF of 15) and protective clothing when using Tretinoin Cream, USP (Emollient). Patients with sunburn should be advised not to use Tretinoin Cream, USP (Emollient) until fully recovered. Patients who may have considerable sun exposure, e.g., due to their occupation and those patients with inherent sensitivity to sunlight, should exercise caution when using Tretinoin Cream, USP (Emollient) and follow the precautions outlined in the Patient Package Insert.

Tretinoin Cream, USP (Emollient) should be kept out of the eyes, mouth, angles of the nose, and mucous membranes. Topical use may cause severe local erythema, pruritus, burning, stinging, and peeling at the site of application. If the degree of local irritation warrants, patients should be directed to use less medication, decrease the frequency of application, discontinue use temporarily, or discontinue use altogether and consider additional appropriate therapy.

Tretinoin has been reported to cause severe irritation on eczematous skin and should be used only with caution in patients with this condition.

Application of larger amounts of medication than recommended has not been shown to lead to more rapid or better results, and marked redness, peeling, or discomfort may occur.

PRECAUTIONS

General

Tretinoin Cream, USP (Emollient) should only be used as an adjunct to a comprehensive skin care and sunlight avoidance program. (see INDICATIONS AND USAGE section.)

If a drug sensitivity, chemical irritation, or a systemic adverse reaction develops, use of Tretinoin Cream, USP (Emollient) should be discontinued.

Weather extremes, such as wind or cold, may be more irritating to patients using tretinoin-containing products.

Information for Patients

Tretinoin Cream, USP (Emollient) 0.05% is to be used as described below unless otherwise directed by your physician:

1. It is for use on the face only.
2. Avoid contact with the eyes, ears, nostrils, angles of the nose, and mouth. Tretinoin Cream, USP (Emollient) may cause severe redness, itching, burning, stinging, and peeling if used on these areas.
3. In the evening, gently wash your face with a mild soap. Pat skin dry and wait 20-30 minutes before applying Tretinoin Cream, USP (Emollient). Apply only a pea-sized amount of Tretinoin Cream, USP (Emollient) to your face at one time. This should be enough to cover the entire affected area lightly.
4. Do not wash your face for at least one hour after applying Tretinoin Cream, USP (Emollient).
5. For best results, you are advised not to apply another skin care product or cosmetic for at least one hour after applying Tretinoin Cream, USP (Emollient).
6. In the morning, apply a moisturizing sunscreen, SPF 15 or greater.
7. Tretinoin Cream, USP (Emollient) is a serious medication. Do not use Tretinoin Cream, USP (Emollient) if you are pregnant or attempting to become pregnant. If you become pregnant while using Tretinoin Cream, USP (Emollient), please contact your physician immediately.
8. Avoid sunlight and other medicines that may increase your sensitivity to sunlight.
9. Tretinoin Cream, USP (Emollient) does not remove wrinkles or repair sun-damaged skin.

Please refer to the Patient Package Insert for additional patient information.

Drug Interactions

Concomitant topical medications, medicated or abrasive soaps, shampoos, cleansers, cosmetics with a strong drying effect, products with high concentrations of alcohol, astringents, spices or lime, permanent wave solutions, electrolysis, hair depilatories or waxes, and products that may irritate the skin should be used with caution in patients being treated with Tretinoin Cream, USP (Emollient) because they may increase irritation with Tretinoin Cream, USP (Emollient).

Tretinoin Cream, USP (Emollient) should not be administered if the patient is also taking drugs known to be photosensitizers (e.g., thiazides, tetracyclines, fluoroquinolones, phenothiazines, sulfonamides) because of the possibility of augmented phototoxicity.

Carcinogenesis, Mutagenesis, Impairment of Fertility

In a 91-week dermal study in which CD-1 mice were administered 0.017% and 0.035% formulations of tretinoin, cutaneous squamous cell carcinomas and papillomas were observed in some female mice. These concentrations are lower than the concentration of tretinoin in this clinical formulation (0.05%). A dose-related incidence of liver tumors in male mice was observed at those same doses. The maximum systemic doses associated with the 0.017% and 0.035% formulations are 0.5 and 1.0 mg/kg/day. These doses are 4 and 8 times the maximum human systemic dose, when adjusted for total body surface area. The biological significance of the neoplastic findings is not clear because they occurred at doses that exceeded the maximally tolerated dermal dose of tretinoin and because they were within the background natural occurrence rate for these tumors in this strain of mice. There was no evidence of carcinogenic potential when 0.025 mg/kg/day of tretinoin was administered topically to mice (1/5th of times the maximum human systemic dose, adjusted for total body surface area). For purposes of comparisons of the systemic animal exposure to the systemic human exposure, the maximum human systemic dose is 1 gram of Tretinoin Cream, USP (Emollient) 0.05% applied daily to a 50 kg person (0.01 mg tretinoin/kg body weight, or 0.37 mg/m^2 total body surface area).

Studies in hairless albino mice suggest that concurrent exposure to tretinoin may enhance the tumorigenic potential of carcinogenic doses of UVB and UVA light from a solar simulator. This effect has been confirmed in a later study in pigmented mice, and dark pigmentation did not overcome the enhancement of photocarcinogenesis by 0.05% tretinoin. Although the significance of these studies in humans is not clear, patients should minimize exposure to sunlight or artificial ultraviolet irradiation sources.

The mutagenic potential of tretinoin was evaluated in the Ames assay and in the in vivo mouse micronucleus assay, both of which were negative.

In dermal Segment I fertility studies in rats, slight (not statistically significant) decreases in sperm count and motility were seen at 0.5 mg/kg/day (8 times the maximum human systemic dose adjusted for total body surface area), and slight (not statistically significant) increases in the number and percent of nonviable embryos in females treated with 0.25 mg/kg/day (4 times the maximum human systemic dose adjusted for total body surface area) and above were observed. A dermal Segment III study with Tretinoin Cream, USP (Emollient) has not been performed in any species. In oral Segment I and Segment III studies in rats with tretinoin, decreased survival of neonates and growth retardation were observed at doses in excess of 2 mg/kg/day (>33 times the maximum human systemic dose adjusted for total body surface area).

Pregnancy

Error

Teratogenic effects: Pregnancy Category C.

ORAL tretinoin has been shown to be teratogenic in rats, mice, rabbits, hamsters, and subhuman primates. It was teratogenic and fetotoxic in Wistar rats when given orally or topically in doses greater than 1 mg/kg/day (17 times the maximum human systemic dose normalized for total body surface area). However, variations in teratogenic doses among various strains of rats have been reported. In the cynomolgus monkey, which, metabolically, is closer to humans for tretinoin than the other species examined, fetal malformations were reported at doses of 10 mg/kg/day or greater, but none were observed at 5 mg/kg/day (167 times the maximum human systemic dose adjusted for total body surface area), although increased skeletal variations were observed at all doses. A dose-related increase in embryolethality and abortion was reported. Similar results have also been reported in pigtail macaques.

TOPICAL tretinoin in animal teratogenicity tests has generated equivocal results. There is evidence for teratogenicity (shortened or kinked tail) of topical tretinoin in Wistar rats at doses greater than 1 mg/kg/day (17 times the maximum human systemic dose adjusted for total body surface area). Anomalies (humerus: short 13%, bent 6%, os parietal incompletely ossified 14%) have also been reported when 10 mg/kg/day was dermally applied.

There are other reports in New Zealand White rabbits administered doses of greater than 0.2 mg/kg/day (7 times the maximum human systemic dose adjusted for total body surface area) of an increased incidence of domed head and hydrocephaly, typical of retinoid-induced fetal malformations in this species.

In contrast, several well-controlled animal studies have shown that dermally applied tretinoin may be fetotoxic, but not overtly teratogenic, in rats and rabbits at doses of 1.0 and 0.5 mg/kg/day, respectively (17 times the maximum human systemic dose adjusted for total body surface area in both species).

With widespread use of any drug, a small number of birth defect reports associated temporally with the administration of the drug would be expected by chance alone. Thirty human cases of temporally-associated congenital malformations have been reported during twenty-five years of clinical use of another formulation of topical tretinoin (Retin-A). Although no definite pattern of teratogenicity and no causal association has been established from these cases, 5 of the reports describe the rare birth defect category holoprosencephaly (defects associated with incomplete midline development of the forebrain). The significance of these spontaneous reports in terms of risk to the fetus is not known.

Non-teratogenic effects

Dermal tretinoin has been shown to be fetotoxic in rabbits when administered 0.5 mg/kg/day (17 times the human topical dose normalized for total body surface area). Oral tretinoin has been shown to be fetotoxic, resulting in skeletal variations and increased intrauterine death, in rats when administered 2.5 mg/kg/day (42 times the maximum human systemic dose adjusted for total body surface area).

There are, however, no adequate and well-controlled studies in pregnant women. Tretinoin Cream, USP (Emollient) should not be used during pregnancy.

Nursing Mothers

It is not known whether this drug is excreted in human milk. Since many drugs are excreted in human milk, mitigation of fine wrinkles, mottled hyperpigmentation, and tactile roughness on the face with Tretinoin Cream, USP (Emollient) may be postponed in nursing mothers until after completion of the nursing period.

Pediatric Use

Safety and effectiveness in patients less than 18 years of age have not been established.

Geriatric Use

Clinical studies of Tretinoin Cream, USP (Emollient) 0.05% did not include a sufficient number of subjects aged 65 and over to determine whether they respond differently than younger subjects. Other reported clinical experience has not identified differences in responses between elderly and younger patients.

ADVERSE REACTIONS

(see WARNINGS and PRECAUTIONS sections.)

In double-blind, vehicle-controlled studies involving 179 patients who applied Tretinoin Cream, USP (Emollient) 0.05% to their faces, adverse reactions associated with the use of Tretinoin Cream, USP (Emollient) 0.05% were limited primarily to the skin. During these trials, 4% of patients had to discontinue use of Tretinoin Cream, USP (Emollient) 0.05% because of adverse reactions. These discontinuations were due to skin irritation or related cutaneous adverse reactions.

Local reactions such as peeling, dry skin, burning, stinging, erythema, and pruritus were reported by almost all subjects during therapy with Tretinoin Cream, USP (Emollient) 0.05%. These signs and symptoms were usually of mild to moderate severity and generally occurred early in therapy. In most patients the dryness, peeling, and redness recurred after an initial (24 week) decline.

In spontaneous post-marketing adverse event reporting for Tretinoin Cream, USP (Emollient) 0.05%, approximately 2% of those were for skin hypo- or hyperpigmentation. Other spontaneously reported adverse events predominantly appear to be local reactions similar to those seen in clinical trials.

OVERDOSAGE

Application of larger amounts of medication than recommended has not been shown to lead to more rapid or better results, and marked redness, peeling, or discomfort may occur. Oral ingestion of the drug may lead to the same side effects as those associated with excessive oral intake of Vitamin A.

DOSAGE AND ADMINISTRATION

- Do NOT use Tretinoin Cream, USP (Emollient) if the patient is pregnant or is attempting to become pregnant or is at high risk of pregnancy
- Do NOT use Tretinoin Cream, USP (Emollient) if the patient is sunburned or if the patient has eczema or other chronic skin conditions of the face
- Do NOT use Tretinoin Cream, USP (Emollient) if the patient is inherently sensitive to sunlight
- Do NOT use Tretinoin Cream, USP (Emollient) if the patient is also taking drug(s) known to be photosensitizers (e.g., thiazides, tetracyclines, fluoroquinolones, phenothiazines, sulfonamides) because of the possibility of augmented phototoxicity.

Patients require detailed instruction to obtain maximal benefits and to understand all the precautions necessary to use this product with greatest safety. The physician should review the Patient Package Insert.

Tretinoin Cream, USP (Emollient) should be applied to the face once a day in the evening, using only enough to cover the entire affected area lightly. Patients should gently wash their faces with a mild soap, pat the skin dry, and wait 20 to 30 minutes before applying Tretinoin Cream, USP (Emollient). The patient should apply a pea-sized amount of cream to cover the entire affected face lightly. Caution should be taken when applying the cream to avoid the eyes, ears, nostrils, and mouth.

Application of Tretinoin Cream, USP (Emollient) may cause a transitory feeling of warmth or slight stinging.

Mitigation (palliation) of facial fine wrinkling, mottled hyperpigmentation, and tactile roughness may occur gradually over the course of therapy. Up to six months of therapy may be required before the effects are seen. Most of the improvement noted with Tretinoin Cream, USP (Emollient) 0.05% is seen during the first 24 weeks of therapy. Thereafter, therapy primarily maintains the improvement realized during the first 24 weeks.

With discontinuation of Tretinoin Cream, USP (Emollient) 0.05% therapy, a majority of patients will lose most mitigating effects of Tretinoin Cream, USP (Emollient) 0.05% on fine wrinkles, mottled hyperpigmentation, and tactile roughness of facial skin; however, the safety and effectiveness of using Tretinoin Cream, USP (Emollient) 0.05% daily for greater than 48 weeks have not been established.

Application of larger amounts of medication than recommended may not lead to more rapid results or better results, and marked redness, peeling, or discomfort may occur.

Patients treated with Tretinoin Cream, USP (Emollient) 0.05% may use cosmetics, but the areas to be treated should be cleansed thoroughly before the medication is applied. (See PRECAUTIONS section.)

HOW SUPPLIED

Tretinoin Cream, USP (Emollient) 0.05% is available in these sizes:

NDC 50224-002-05 40 gram tube
NDC 50224-002-04 60 gram tube

Storage: Store at 20-25°C (68-77°F) [see USP Controlled Room Temperature]. DO NOT FREEZE.

Rx only.

128278

Printed in USA

Manufactured by DPT Laboratories, San Antonio, TX 78215
Distributed by Suneva Medical Inc. San Diego, CA, 92121

SUPPLEMENTAL PATIENT MATERIAL

USE ONLY ON THE FACE

Read this leaflet carefully before you start to use your medicine. Read the information you get every time you get more medicine. There may be new information about the drug. This leaflet does not take the place of talks with your doctor. It is important for you to talk with your doctor about how to use Tretinoin Cream, USP (Emollient) for the best results and how to reduce side effects.

What is the Most Important Information about Tretinoin Cream, USP (Emollient)?

Tretinoin Cream, USP (Emollient) is a serious medicine. Do not use Tretinoin Cream, USP (Emollient) if you are pregnant or attempting to become pregnant. If you become pregnant while using Tretinoin Cream, USP (Emollient), please contact your doctor immediately.

Avoid sunlight and other medicines that may increase your sensitivity to sunlight (See “Who should not use Tretinoin Cream, USP (Emollient)?”).

Tretinoin Cream, USP (Emollient) does not remove wrinkles or repair sun-damaged skin. (See “What is Tretinoin Cream, USP (Emollient)?” for more details.) Tretinoin Cream, USP (Emollient) 0.05% has not been tested in people over age 50 or in people with medium or dark skin color. (See “Who should not use Tretinoin Cream, USP (Emollient)?”).

What is Tretinoin Cream, USP (Emollient) 0.05%?

Tretinoin Cream, USP (Emollient) 0.05% is a prescription medicine that may reduce fine facial wrinkles, facial mottled hyperpigmentation, and facial skin roughness. It is for patients who are also using a skin care and sunlight avoidance program. Tretinoin Cream, USP (Emollient) does not remove wrinkles or repair sun-damaged skin. Tretinoin Cream, USP (Emollient) does not work for everyone who uses it. It may work better for some patients than for others.

Tretinoin Cream, USP (Emollient) should be used only under the guidance of your doctor as part of a skin care and sunlight avoidance program. This program should include avoiding sunlight as much as possible, using clothing to protect you from sunlight, using sunscreens with a minimum SPF of 15, and using face creams that add moisture to the skin.

When you use Tretinoin Cream, USP (Emollient), you will not see improvement right away. Generally, you may notice some effects in 3 to 4 months. If Tretinoin Cream, USP (Emollient) treatment is stopped, the improvement may gradually disappear.

The use of Tretinoin Cream, USP (Emollient) 0.05% in patients for more than 48 weeks has not been studied. Therefore, it is not known if Tretinoin Cream, USP (Emollient) 0.05% is safe or works if used longer than 48 weeks. Tretinoin Cream, USP (Emollient) 0.05% has not been shown to work or be safe in people over age 50, in people with medium to dark skin color, or in people with visible actinic keratoses or in people with a history of skin cancer.

Who should not use Tretinoin Cream, USP (Emollient)?

Do not use Tretinoin Cream, USP (Emollient) if:

- you are pregnant or plan to become pregnant. If you become pregnant while using Tretinoin Cream, USP (Emollient), please contact your doctor immediately.
- you are sunburned or your skin is irritated.
- you are highly sensitive to sunlight.
- you are allergic to any of the ingredients in Tretinoin Cream, USP (Emollient). The active ingredient is tretinoin. Ask your doctor or pharmacist about the inactive ingredients.

Tretinoin Cream, USP (Emollient) can cause increased skin irritation and increased chance of sunburn.

Tell your doctor if you have any skin condition. Tretinoin Cream, USP (Emollient) may not be right for you.

Because Tretinoin Cream, USP (Emollient) may make your skin more likely to burn from sunlight, tell your doctor if you are using other medicines that increase sensitivity to sunlight. You should not use Tretinoin Cream, USP (Emollient) with such medicines. These include, but are not limited to:

- thiazides (to treat high blood pressure)
- tetracyclines, fluoroquinolones, sulfonamides (to treat infection)
- phenothiazines (to treat serious emotional problems)

If you are taking any prescription or non-prescription medicines, check with your doctor to make sure you can use Tretinoin Cream, USP (Emollient) with them.

We do not know if Tretinoin Cream, USP (Emollient) is passed to infants through breast milk. Therefore, tell your doctor if you are breast feeding.

How should I use Tretinoin Cream, USP (Emollient)?

Use Tretinoin Cream, USP (Emollient) as part of a total skin care and sunlight avoidance program. Follow your doctor's instructions on how to use Tretinoin Cream, USP (Emollient). Tretinoin Cream, USP (Emollient) is usually applied to the face once a day in the evening, following the 3 steps listed below:

1. Gently wash your face with a mild soap.
2. Pat the skin dry and wait 20-30 minutes before applying Tretinoin Cream, USP (Emollient).
3. Apply only a pea-sized amount of Tretinoin Cream, USP (Emollient) to the face at one time. It should be enough to cover the affected area lightly.

Be especially careful when applying Tretinoin Cream, USP (Emollient) to avoid your eyes, ears, nostrils, angles of the nose, and mouth. Tretinoin Cream, USP (Emollient) may cause severe redness, itching, burning, stinging, and peeling if used on these areas.

Using too much Tretinoin Cream, USP (Emollient) may increase discomfort and skin redness and peeling.

You may use cosmetics one hour after applying Tretinoin Cream, USP (Emollient). If you do, be sure to clean your face before applying Tretinoin Cream, USP (Emollient) again. Skin moisturizers should be used at least every morning to protect the treated areas from dryness.

Use sunscreen and wear protective clothing to protect the treated areas from sunlight. If you sunburn easily, or if you spend a lot of time exposed to sunlight, be especially careful to protect your skin.

What should I avoid while using Tretinoin Cream, USP (Emollient)?

Tretinoin Cream, USP (Emollient) can make your treated skin more sensitive to sunlight. Therefore, keep out of the sunlight as much as possible and do not use sunlamps. Avoid as much as possible products that can increase skin irritation, such as:

- other skin medicines
- medicated or abrasive (rough) soaps
- permanent wave solutions
- chemical hair removers or waxes
- electrolysis
- products with alcohol, spices, astringents, or lime
- cleansers, shampoos, or cosmetics with a strong drying effect
- other products that may irritate your skin

What are the possible side effects of Tretinoin Cream, USP (Emollient)?

You may feel brief warmth or stinging on your skin after you use Tretinoin Cream, USP (Emollient). Most patients report peeling, dry skin, burning, stinging, itching, and redness. These are usually mild to moderate and occur early in treatment. Contact your doctor if the side effects are a problem.

General advice about prescription medicines

Medicines are sometimes prescribed for conditions that are not mentioned in patient information leaflets. Only use Tretinoin Cream, USP (Emollient) to treat the condition that your doctor has prescribed it for. Do not give Tretinoin Cream, USP (Emollient) to other people. It may harm them.

This leaflet summarizes the most important information about Tretinoin Cream, USP (Emollient). If you would like more information, talk with your doctor. You can ask your pharmacist or doctor for information about Tretinoin Cream, USP (Emollient) that is written for health professionals.

You are encouraged to report negative side effects of prescription drugs to the FDA. Visit www.fda.gov/medwatch, or call 1-800-FDA-1088.

SUNEVA MEDICAL INC.
San Diego, CA 92121

PACKAGE LABEL PRINCIPAL DISPLAY

NDC 50224-002-05 40 gram tube

NDC 50224-002-04 60 gram tube